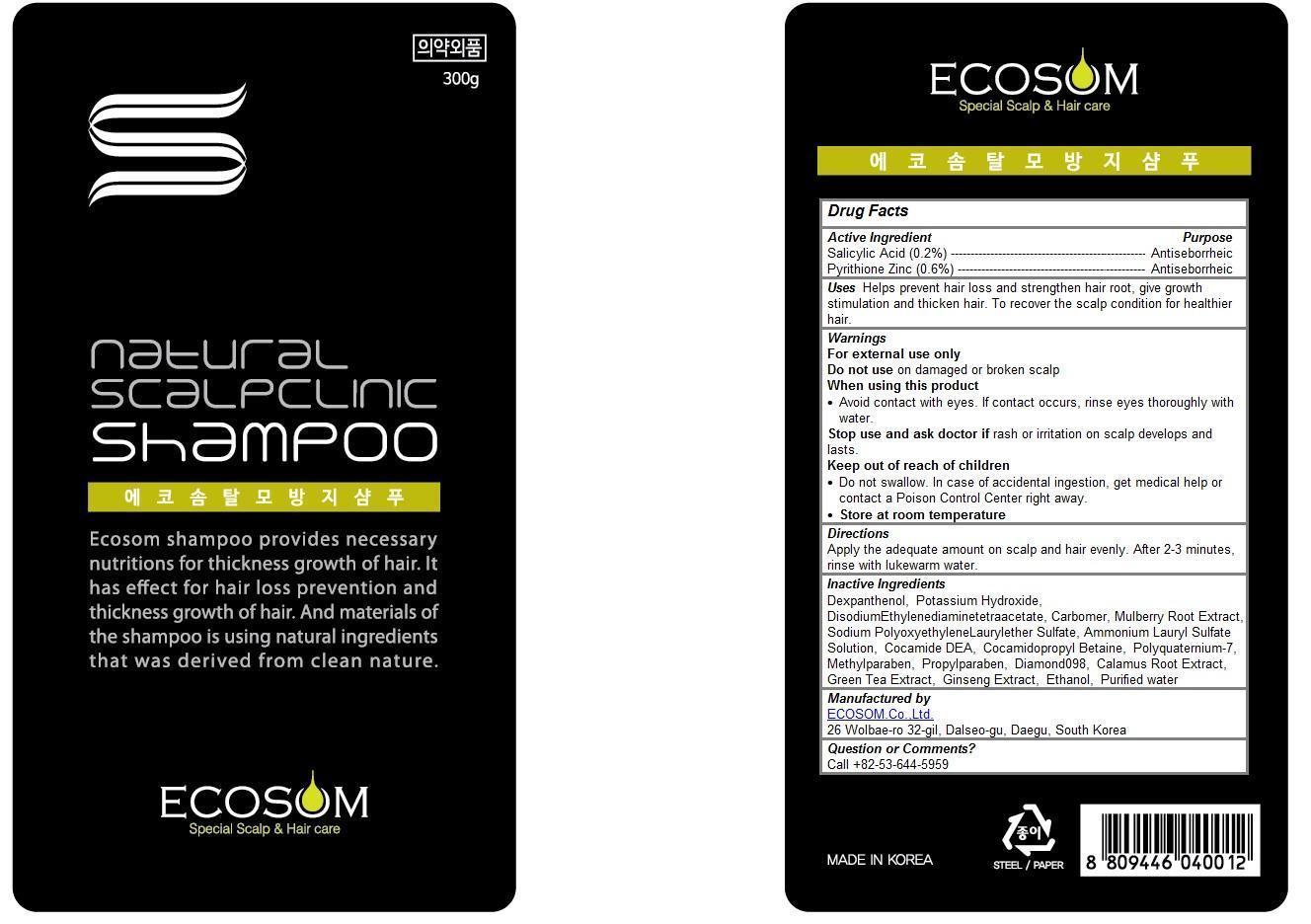 DRUG LABEL: Ecosom
NDC: 69856-101 | Form: SHAMPOO
Manufacturer: ECOSOM.Co.,Ltd.
Category: otc | Type: HUMAN OTC DRUG LABEL
Date: 20150715

ACTIVE INGREDIENTS: SALICYLIC ACID 0.2 1/300 mL; PYRITHIONE ZINC 0.6 1/300 mL
INACTIVE INGREDIENTS: DEXPANTHENOL; POTASSIUM HYDROXIDE; DISODIUM ETHYLENEDIAMINEDIACETATE; CARBOMER 1342; WHITE MULBERRY; SODIUM LAURETH-12 SULFATE; AMMONIUM LAURYL SULFATE; COCO DIETHANOLAMIDE; COCAMIDOPROPYL BETAINE; POLYQUATERNIUM-7 (70/30 ACRYLAMIDE/DADMAC; 1600000 MW); METHYLPARABEN; PROPYLPARABEN; ACORUS CALAMUS ROOT; DIAMOND; GREEN TEA LEAF; ASIAN GINSENG; ALCOHOL; WATER

Ecosom Shampoo